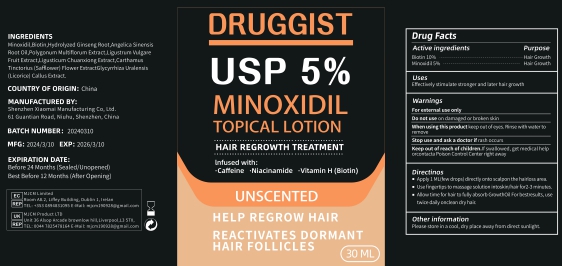 DRUG LABEL: DRUGGIST 5% MINOXIDIL
NDC: 83872-261 | Form: LIQUID
Manufacturer: Shenzhen Xiaomai Manufacturing Co., Ltd.
Category: otc | Type: HUMAN OTC DRUG LABEL
Date: 20240626

ACTIVE INGREDIENTS: BIOTIN 10 g/30 mL; MINOXIDIL 5 g/30 mL
INACTIVE INGREDIENTS: LIGUSTRUM VULGARE WHOLE; ANGELICA ACUTILOBA ROOT; CARTHAMUS TINCTORIUS FLOWER OIL

Active Ingredient

Minoxidil 5%

Biotin 10%

Purpose

Effectively stimulate stronger and later hair growth .

Use

Use to regrow hair on the top of the scalp

Warnings

For external use only
Do not use on damaged or broken skin
When using this product keep out of eyes. Rinse with water to remove.
Stop use and ask a doctor if rash occurs
Keep out of reach of children.If swallowed, get medical help or contacta Poison Control Center right away.

Do not use on damaged or broken skin

When Using

When using this product keep out of eyes. Rinse with water to remove.

Stop Use

Stop use and ask a doctor if rash occurs

Keep Oot Of Reach Of Children

Keep out of reach of children.If swallowed, get medical help or contacta Poison Control Center right away.

Ask Doctor

Stop use and ask a doctor if rash occurs

Directions

1. Apply 1 ML(few drops) directly onto scalp on the hair loss area.
2. Use fingertips to massage solution into skin/hair for2-3 minutes.
3 . Allow time for hair to fully absorb Growth Oil Forbest results, use twice daily on clean dry hair.

Other information

Please store in a cool, dry place away from direct sunlight.

Inactive ingredients

Hydrolyzed Ginseng Root,Angelica Sinensis Root Oil,Polygonum Multiflorum Extract,Ligustrum Vulgare Fruit Extract,Ligusticum Chuanxiong Extract,Carthamus Tinctorius (Safflower) Flower ExtractGlycyrrhiza Uralensis (Licorice) Callus Extract.

Purpose

Hair Regrowth Treatment